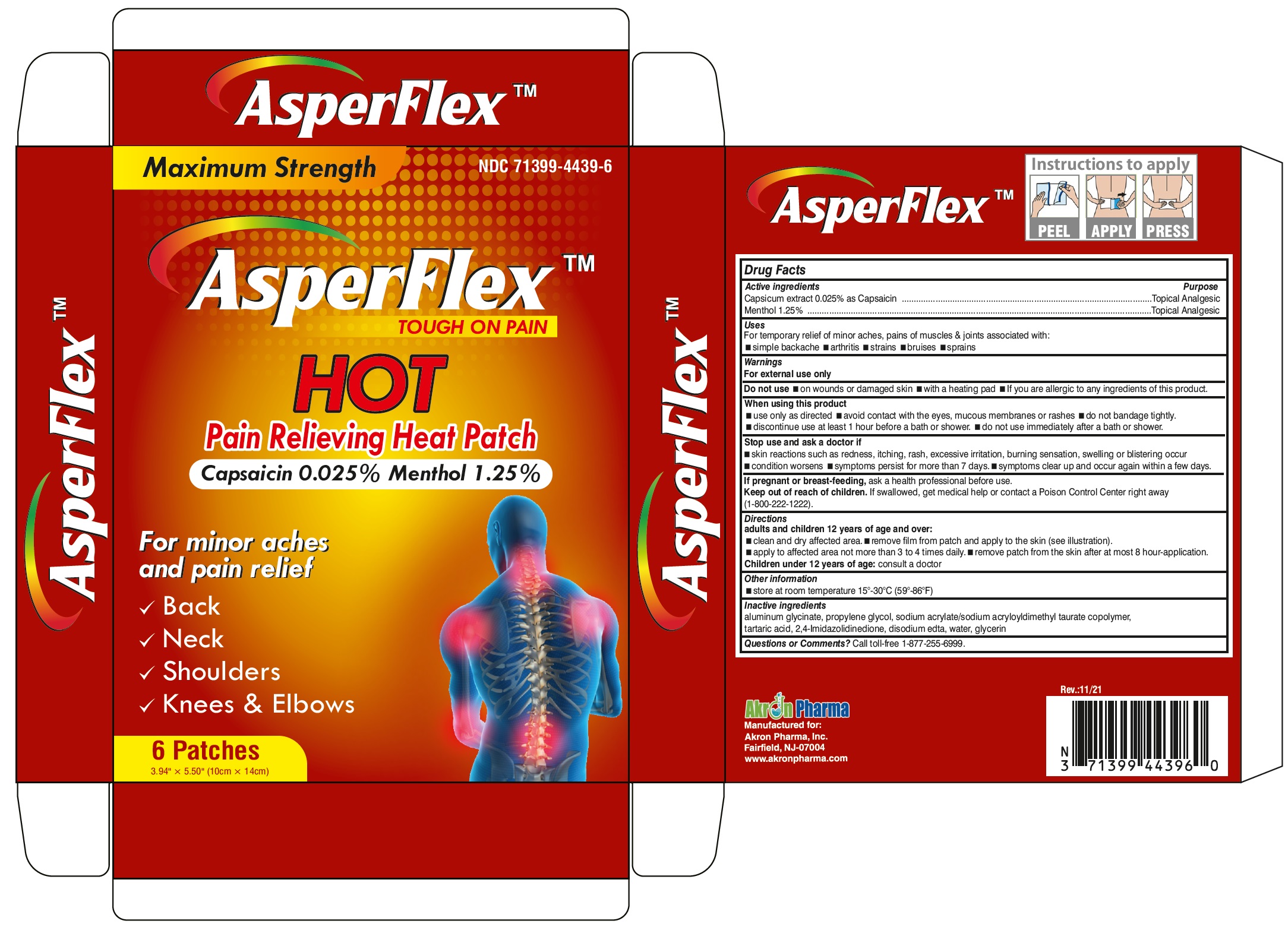 DRUG LABEL: AsperFlex HOT
NDC: 71399-4439 | Form: PATCH
Manufacturer: Akron Pharma Inc.
Category: otc | Type: HUMAN OTC DRUG LABEL
Date: 20251002

ACTIVE INGREDIENTS: CAPSICUM 0.025 g/100 g; MENTHOL 1.25 g/100 g
INACTIVE INGREDIENTS: DIHYDROXYALUMINUM AMINOACETATE ANHYDROUS; PROPYLENE GLYCOL; SODIUM ACRYLATE; TARTARIC ACID; HYDANTOIN; EDETATE DISODIUM ANHYDROUS; WATER; GLYCERIN

AsperFlex
Tough on Pain
HOT Pain Relieving Patch

Active ingredients

Capsicum extract 0.025% as Capsaicin
Menthol 1.25%

Purpose

Topical analgesic

Uses

For temporary relief of minor aches and pains of muscles and joints associated with:

- arthritis
- simple backache
- strains
- bruises
- sprains

Warnings

For external use only

Do not use

- on wounds or damaged skin
- with a heating pad
- if you are allergic to any ingredients of this product

When using this product

- use only as directed
- avoid contact with the eyes, mucous membranes or rashes
- do not bandage tightly

Stop use and ask a doctor if

- rash, itching or excessive skin irritation develops
- contisions worsen
- symptoms persist for more than 7 days
- symptoms clear up and occur again within a few days

If pregnant or breast-feeding,

ask a health professional before use.

Keep out of reach of children.

If swallowed, get medical help or contact a Poison Control Center right away. (1-800-222-1222).

Directions

Adults and children 12 years of age and over:

- clean and dry affected area
- remove patch from film
- apply to affected area not more than 3 to 4 times daily
- remove patch from the skin after at most 8-hour application

Children under 12 years of age:consult a doctor

Other information

- store at room temperature 15°-30°C (59°-86°F).

Inactive ingredients

aluminum glycinate, propylene glycol, sodium acrylate/sodium acryloyldimethyl taurate copolymer, tartaric acid, 2,4-Imidazolidinedione, disodium edta, water, glycerin

Questions or comments?

Call toll-free 1-877-255-6999.

Manufactured for:
Akron Pharma, Inc.
Fairfield, NJ 07004

www.akronpharma.com